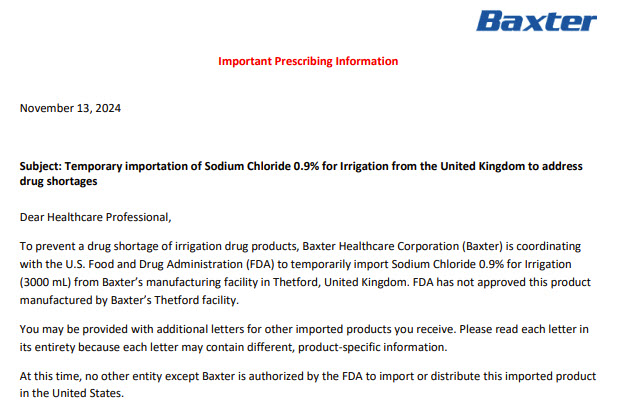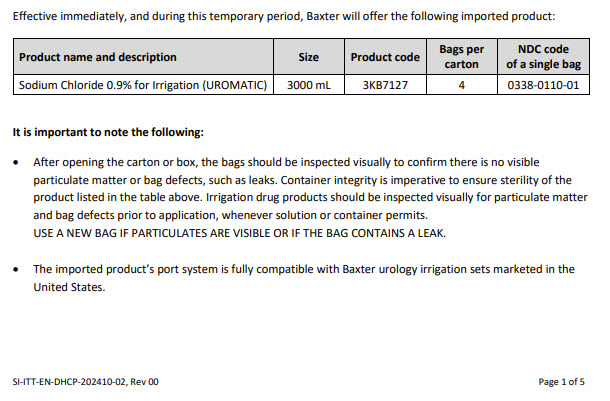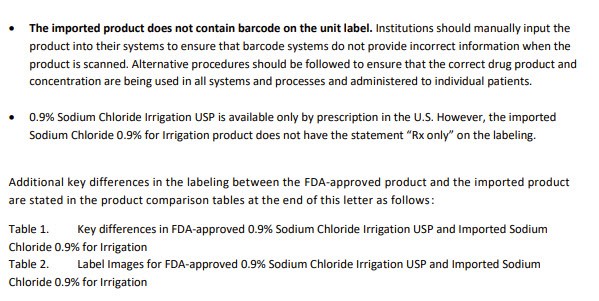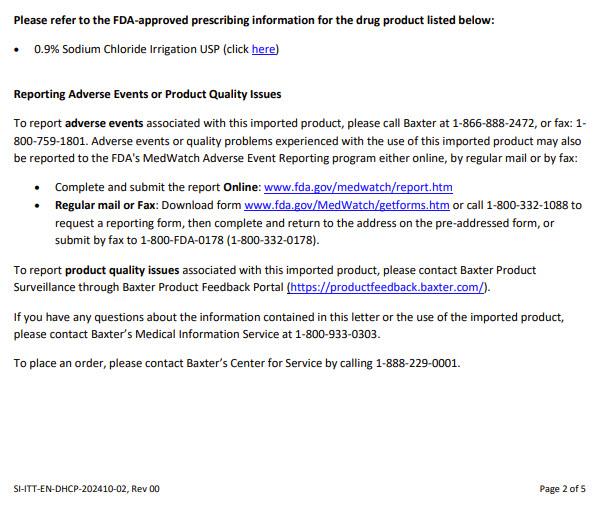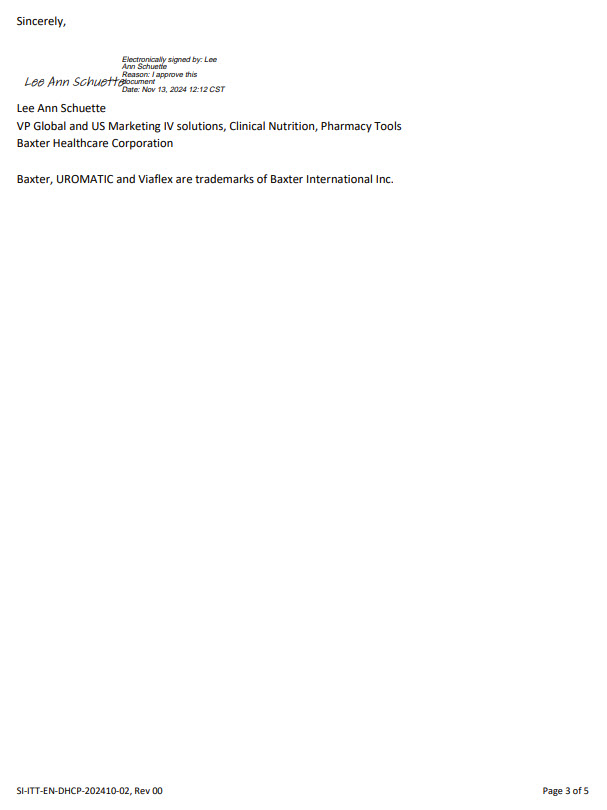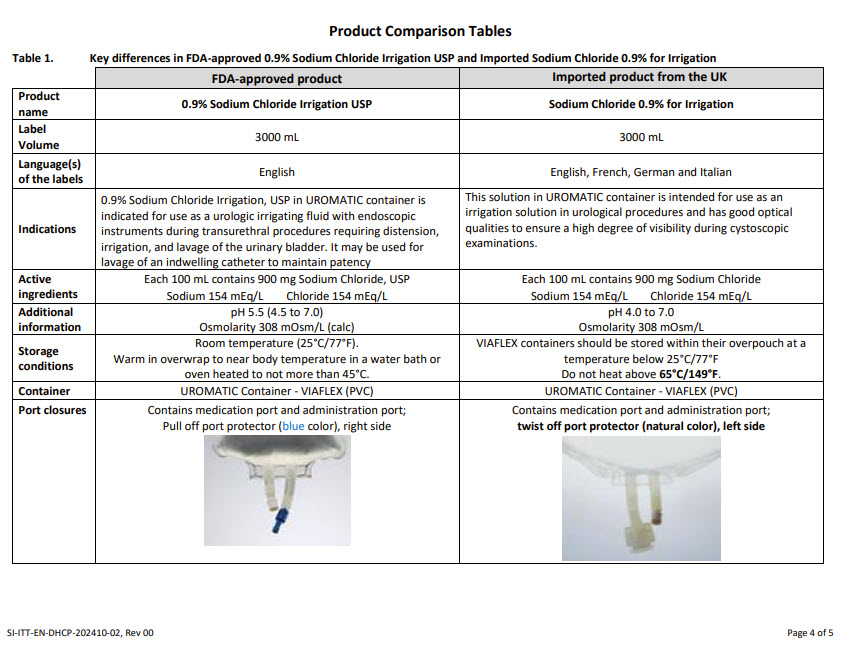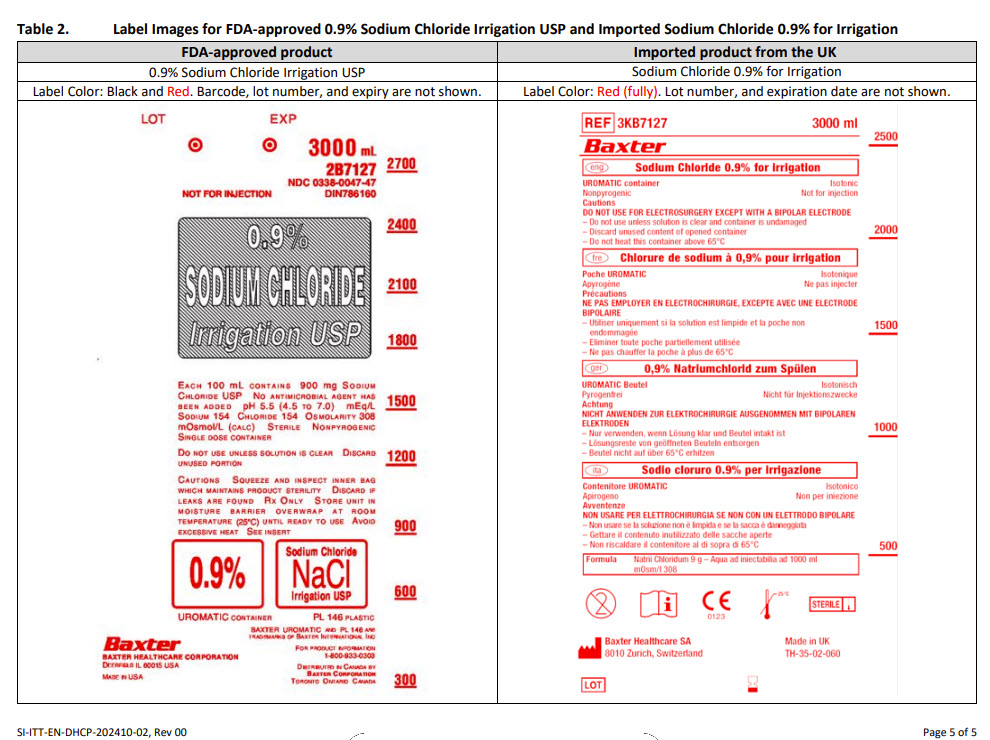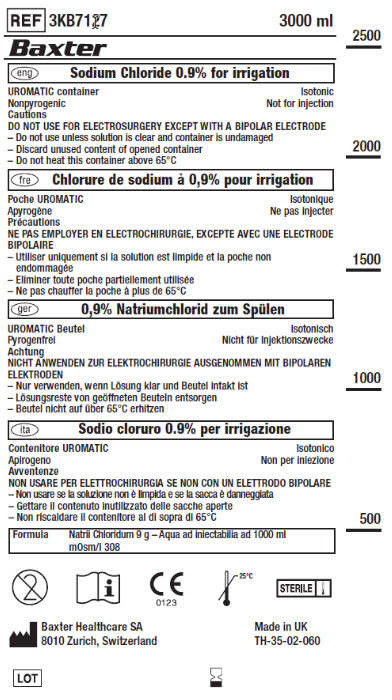 DRUG LABEL: Sodium Chloride
NDC: 0338-0110 | Form: IRRIGANT
Manufacturer: Baxter Healthcare Company
Category: prescription | Type: HUMAN PRESCRIPTION DRUG LABEL
Date: 20241113

ACTIVE INGREDIENTS: SODIUM CHLORIDE 900 mg/100 mL

Sodium chloride 0.9% for irrigation

Health Care Provider Letter

Please refer to the FDA-approved prescribing information for the drug product listed below:
• 0.9% Sodium Chloride Irrigation USP (click https://dailymed.nlm.nih.gov/dailymed/drugInfo.cfm?setid=886f889b-f3cf-4197-b307-6cfa88c89436)

• Complete and submit the report Online: www.fda.gov/medwatch/report.htm
• Regular mail or Fax: Download form www.fda.gov/MedWatch/getforms.htm or call 1-800-332-1088 to request a reporting form, then complete and return to the address on the pre-addressed form, or submit by fax to 1-800-FDA-0178 (1-800-332-0178).

To report productqualityissues associated with this imported product, please contact Baxter Product Surveillance through Baxter Product Feedback Portal (https://productfeedback.baxter.com/)

PACKAGE/LABEL PRINCIPAL DISPLAY PANEL

Container Label

REF 3KB7127 3000 ml

Baxter Logo

eng Sodium Chloride 0.9% for irrigation
UROMATIC container
Isotonic
Nonpyrogenic
Not for injection
Cautions
DO NOT USE FOR ELECTROSURGERY EXCEPT WITH A BIPOLER ELECTRODE
- Do not use unless solution is clear and container is undamaged
- Discard unused content of opened container
- Do not heat this container above 65°C

fre Chlorure de sodium à 0,9% pour irrigation

ger 0,9% Natriumchlorid zum Spülen

ita Sodio cloruro 0.9% per irrigazione

Formula
Natril Chloridum 9 g – Aqua ad injectabilia ad 1000 ml
mOsm/l 308

Do Not Re-Use Symbol
Consult Instructions for Use Symbol
European Conformity Symbol
Temperature Limit 25°C Symbol
Sterile Symbol

Manufacturer Symbol
Baxter Healthcare SA
8010 Zurich, Switzerland

Made in UK
TH-35-02-060

Lot Symbol
Use-by Date Symbol

2500

2000

1500

1000

500